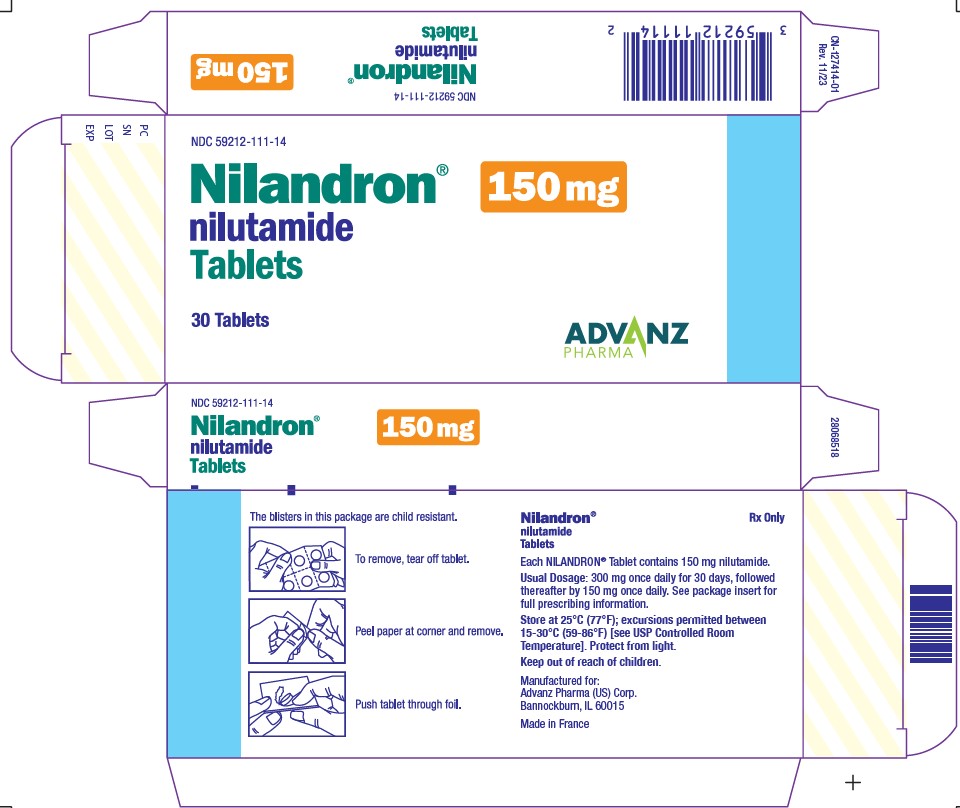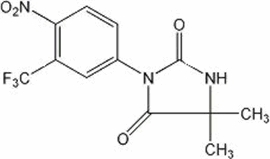 DRUG LABEL: Nilandron
NDC: 59212-111 | Form: TABLET
Manufacturer: Advanz Pharma (US) Corp.
Category: prescription | Type: Human Prescription Drug Label
Date: 20251212

ACTIVE INGREDIENTS: Nilutamide 150 mg/1 1
INACTIVE INGREDIENTS: STARCH, CORN; LACTOSE; DOCUSATE SODIUM; MAGNESIUM STEARATE; TALC; POVIDONE

NILANDRON®
(nilutamide)
Tablets

DESCRIPTION

NILANDRON® tablets contain nilutamide, a nonsteroidal, orally active antiandrogen having the chemical name 5,5-dimethyl-3-[4-nitro-3-(trifluoromethyl)phenyl]-2,4-imidazolidinedione with the following structural formula:

Nilutamide is a microcrystalline, white to practically white powder with a molecular weight of 317.25. Its molecular formula is C12H10F3N3O4.

It is freely soluble in ethyl acetate, acetone, chloroform, ethyl alcohol, dichloromethane, and methanol. It is slightly soluble in water [<0.1% W/V at 25°C (77°F)]. It melts between 153°C and 156°C (307.4°F and 312.8°F).

Each NILANDRON tablet contains 150 mg of nilutamide. Other ingredients in NILANDRON tablets are corn starch, lactose, povidone, docusate sodium, magnesium stearate, and talc.

CLINICAL PHARMACOLOGY

Mechanism of Action

Prostate cancer is known to be androgen sensitive and responds to androgen ablation. In animal studies, nilutamide has demonstrated antiandrogenic activity without other hormonal (estrogen, progesterone, mineralocorticoid, and glucocorticoid) effects. In vitro, nilutamide blocks the effects of testosterone at the androgen receptor level. In vivo, nilutamide interacts with the androgen receptor and prevents the normal androgenic response.

Pharmacokinetics

Absorption:

Analysis of blood, urine, and feces samples following a single oral 150-mg dose of [^14C]-nilutamide in patients with metastatic prostate cancer showed that the drug is rapidly and completely absorbed and that it yields high and persistent plasma concentrations.

Distribution:

After absorption of the drug, there is a detectable distribution phase. There is moderate binding of the drug to plasma proteins and low binding to erythrocytes. The binding is nonsaturable except in the case of alpha-1-glycoprotein, which makes a minor contribution to the total concentration of proteins in the plasma. The results of binding studies do not indicate any effects that would cause nonlinear pharmacokinetics.

Metabolism:

The results of a human metabolism study using ^14C-radiolabelled tablets show that nilutamide is extensively metabolized and less than 2% of the drug is excreted unchanged in urine after 5 days. Five metabolites have been isolated from human urine. Two metabolites display an asymmetric center, due to oxidation of a methyl group, resulting in the formation of D- and L-isomers. One of the metabolites was shown, in vitro, to possess 25 to 50% of the pharmacological activity of the parent drug, and the D-isomer of the active metabolite showed equal or greater potency compared to the L-isomer. However, the pharmacokinetics and the pharmacodynamics of the metabolites have not been fully investigated.

Elimination:

The majority (62%) of orally administered [^14C]-nilutamide is eliminated in the urine during the first 120 hours after a single 150-mg dose. Fecal elimination is negligible, ranging from 1.4% to 7% of the dose after 4 to 5 days. Excretion of radioactivity in urine likely continues beyond 5 days. The mean elimination half-life of nilutamide determined in studies in which subjects received a single dose of 100–300 mg ranged from 38.0 to 59.1 hours with most values between 41 and 49 hours. The elimination of at least one metabolite is generally longer than that of unchanged nilutamide (59–126 hours). During multiple dosing of 150 mg nilutamide (given as 3 × 50 mg) twice a day, steady state was reached within 2 to 4 weeks for most patients, and mean steady state AUC0–12 was 110% higher than the AUC0–∞ obtained from the first 150 mg dose. These data and in vitro metabolism data suggest that, upon multiple dosing, metabolic enzyme inhibition may occur for this drug.

Clinical Studies

Nilutamide through its antiandrogenic activity can complement surgical castration, which suppresses only testicular androgens. The effects of the combined therapy were studied in patients with previously untreated metastatic prostate cancer.

In a double-blind, randomized, multicenter study that enrolled 457 patients (225 treated with orchiectomy and NILANDRON, 232 treated with orchiectomy and placebo), the NILANDRON group showed a statistically significant benefit in time to progression and time to death. The results are summarized below.

 | NILANDRON | PLACEBO
Median Survival (months) | 27.3 | 23.6
Progression-Free Survival (months) | 21.1 | 14.9
Complete or Partial Regression | 41% | 24%
Improvement in Bone Pain | 54% | 37%

INDICATIONS AND USAGE

Metastatic Prostate Cancer

NILANDRON tablets are indicated for use in combination with surgical castration for the treatment of metastatic prostate cancer (Stage D2).

For maximum benefit, NILANDRON treatment must begin on the same day as or on the day after surgical castration.

CONTRAINDICATIONS

NILANDRON tablets are contraindicated:

- in patients with severe hepatic impairment (baseline hepatic enzymes should be evaluated prior to treatment)
- in patients with severe respiratory insufficiency
- in patients with hypersensitivity to nilutamide or any component of this preparation.

WARNINGS

Interstitial Pneumonitis

Interstitial pneumonitis has been reported in 2% of patients in controlled clinical trials in patients exposed to nilutamide. A small study in Japanese subjects showed that 8 of 47 patients (17%) developed interstitial pneumonitis. Reports of interstitial changes including pulmonary fibrosis that led to hospitalization and death have been reported rarely post-marketing. Symptoms included exertional dyspnea, cough, chest pain, and fever. X-rays showed interstitial or alveolo-interstitial changes, and pulmonary function tests revealed a restrictive pattern with decreased DLco. Most cases occurred within the first 3 months of treatment with NILANDRON, and most reversed with discontinuation of therapy.
A routine chest X-ray should be performed prior to initiating treatment with NILANDRON. Baseline pulmonary function tests may be considered. Patients should be instructed to report any new or worsening shortness of breath that they experience while on NILANDRON. If symptoms occur, NILANDRON should be immediately discontinued until it can be determined if the symptoms are drug related.

Hepatitis

Rare cases of death or hospitalization due to severe liver injury have been reported post-marketing in association with the use of NILANDRON. Hepatotoxicity in these reports generally occurred within the first 3 to 4 months of treatment. Hepatitis or marked increases in liver enzymes leading to drug discontinuation occurred in 1% of NILANDRON patients in controlled clinical trials.
Serum transaminase levels should be measured prior to starting treatment with NILANDRON, at regular intervals for the first 4 months of treatment, and periodically thereafter. Liver function tests should also be obtained at the first sign or symptom suggestive of liver dysfunction, e.g. nausea, vomiting, abdominal pain, fatigue, anorexia, "flu-like" symptoms, dark urine, jaundice or right upper quadrant tenderness. If at any time, a patient has jaundice or their ALT rises above 2 times the upper limit of normal, NILANDRON should be immediately discontinued with close followup of liver function tests until resolution.

Use in Women

NILANDRON has no indication for women, and should not be used in this population, particularly for non-serious or non-life threatening conditions.

Other

Foreign postmarketing surveillance has revealed isolated cases of aplastic anemia in which a causal relationship with NILANDRON could not be ascertained.

PRECAUTIONS

General

Antiandrogen Withdrawal Syndrome

Patients whose disease progresses while being treated with an antiandrogen may experience clinical improvement with discontinuation of the antiandrogen.

Information for Patients

Patients should be informed that NILANDRON tablets should be started on the day of or on the day after, surgical castration. They should also be informed that they should not interrupt their dosing of NILANDRON or stop taking this medication without consulting their physician.

Because of the possibility of interstitial pneumonitis, patients should also be told to report immediately any dyspnea or aggravation of pre-existing dyspnea.

Because of the possibility of hepatitis, patients should be told to consult with their physician should nausea, vomiting, abdominal pain or jaundice occur.

Because of the possibility of an intolerance to alcohol (facial flushes, malaise, hypotension) following ingestion of NILANDRON, it is recommended that intake of alcoholic beverages be avoided by patients who experience this reaction. This effect has been reported in about 5% of patients treated with NILANDRON.

In clinical trials, 13% to 57% of patients receiving NILANDRON reported a delay in adaptation to dark, ranging from seconds to a few minutes, when passing from a lighted area to a dark area. This effect sometimes does not abate as drug treatment is continued. Patients who experience this effect should be cautioned about driving at night or through tunnels. This effect can be alleviated by the wearing of tinted glasses.

Drug Interactions

In vitro, nilutamide has been shown to inhibit the activity of liver cytochrome P-450 isoenzymes and, therefore, may reduce the metabolism of compounds requiring these systems.

Consequently, drugs with a low therapeutic margin, such as vitamin K antagonists, phenytoin, and theophylline, could have a delayed elimination and increases in their serum half-life leading to a toxic level. The dosage of these drugs or others with a similar metabolism may need to be modified if they are administered concomitantly with nilutamide. For example, when vitamin K antagonists are administered concomitantly with nilutamide, prothrombin time should be carefully monitored and, if necessary, the dosage of vitamin K antagonists should be reduced.

Carcinogenesis, Mutagenesis, Impairment of Fertility

Administration of nilutamide to rats for 18 months at doses of 0, 5, 15, or 45 mg/kg/day produced benign Leydig cell tumors in 35% of the high-dose male rats (AUC exposures in high-dose rats were approximately 1–2 times human AUC exposures with therapeutic doses). The increased incidence of Leydig cell tumors is secondary to elevated luteinizing hormone (LH) concentrations resulting from loss of feedback inhibition at the pituitary. Elevated LH and testosterone concentrations are not observed in castrated men receiving NILANDRON. Nilutamide had no effect on the incidence, size or time of onset of any spontaneous tumor in rats.

Nilutamide displayed no mutagenic effects in a variety of in vitro and in vivo tests (Ames test, mouse micronucleus test, and two chromosomal aberration tests).

In reproduction studies in rats, nilutamide had no effect on the reproductive function of males and females, and no lethal, teratogenic or growth-suppressive effects on fetuses were found. The maximal dose at which nilutamide did not affect reproductive function in either sex or have an effect on fetuses was estimated to be 45 mg/kg orally (AUC exposures in rats approximately 1–2 times human therapeutic AUC exposures).

Pregnancy

Animal reproduction studies have not been conducted with nilutamide. It is also not known whether nilutamide can cause fetal harm when administered to a pregnant woman or can affect reproductive capacity. Nilutamide should be given to a pregnant woman only if clearly needed.

Pediatric Use

Safety and effectiveness in pediatric patients have not been determined.

Animal Pharmacology and Toxicology

Administration of NILANDRON to beagle dogs resulted in drug-related deaths at dose levels that produce AUC exposures in dogs much lower than the AUC exposures of men receiving the therapeutic doses of 150 and 300 mg/day. Nilutamide-induced toxicity in dogs was cumulative with progressively lower doses producing death when given for longer durations. Nilutamide given to dogs at 60 mg/kg/day (1–2 times human AUC exposure) for 1 month produced 100% mortality. Administration of 20 and 30 mg/kg/day nilutamide (1/2–1 times human AUC exposure) for 6 months resulted in 20% and 70% mortality in treated dogs. Administration to dogs of 3, 6, and 12 mg/kg/day nilutamide (1/10–1/2 human AUC exposure) for 1 year resulted in 8%, 33%, and 50% mortality, respectively. A "no-effect level" for nilutamide-induced mortality in dogs was not identified. Pathology data from the one-year oral toxicity study suggest that the deaths in dogs were secondary to liver toxicity. Marked-to-massive hepatocellular swelling and vacuolization were observed in affected dogs. Liver toxicity in dogs was not consistently associated with elevations of liver enzymes.

Administration of nilutamide to rats at a dose level of 45 mg/kg/day (AUC exposure in rats 1–2 times human therapeutic AUC exposures) for 18 months increased the incidence of lung pathology (granulomatous inflammation and chronic alveolitis).

The hepatic and pulmonary adverse effects observed in nilutamide-treated animals and men are similar to effects observed with another nitroaromatic compound, nitrofurantoin. Nilutamide and nitrofurantoin are both metabolized in vitro to nitroanion free-radicals by microsomal NADPH-cytochrome P450 reductase in the lungs and liver of rats and humans.

ADVERSE REACTIONS

Clinical Trial Experience

The following adverse experiences were reported during a multicenter clinical trial comparing NILANDRON + surgical castration versus placebo + surgical castration. The most frequently reported (greater than 5%) adverse experiences during treatment with NILANDRON tablets in combination with surgical castration are listed below. For comparison, adverse experiences seen with surgical castration and placebo are also listed.

Adverse Experience | NILANDRON + surgical castration (N=225) % All | Placebo + surgical castration (N=232) % All
Cardiovascular System
Hypertension | 5.3 | 2.6
Digestive System
Nausea | 9.8 | 6.0
Constipation | 7.1 | 3.9
Endocrine System
Hot flushes | 28.4 | 22.4
Metabolic and Nutritional System
Increased AST | 8.0 | 3.9
Increased ALT | 7.6 | 4.3
Nervous System
Dizziness | 7.1 | 3.4
Respiratory System
Dyspnea | 6.2 | 7.3
Special Senses
Impaired adaptation to dark | 12.9 | 1.3
Abnormal vision | 6.7 | 1.7
Urogenital System
Urinary tract infection | 8.0 | 9.1

The overall incidence of adverse experiences was 86% (194/225) for the NILANDRON group and 81% (188/232) for the placebo group.

The following adverse experiences were reported during a multicenter clinical trial comparing NILANDRON + leuprolide versus placebo + leuprolide. The most frequently reported (greater than 5%) adverse experiences during treatment with NILANDRON tablets in combination with leuprolide are listed below. For comparison, adverse experiences seen with leuprolide and placebo are also listed.

Adverse Experience | NILANDRON + leuprolide (N=209) % All | Placebo + leuprolide (N=202) % All
Body as a Whole
Pain | 26.8 | 27.7
Headache | 13.9 | 10.4
Asthenia | 19.1 | 20.8
Back pain | 11.5 | 16.8
Abdominal pain | 10.0 | 5.4
Chest pain | 7.2 | 4.5
Flu syndrome | 7.2 | 3.0
Fever | 5.3 | 6.4
Cardiovascular System
Hypertension | 9.1 | 9.9
Digestive System
Nausea | 23.9 | 8.4
Constipation | 19.6 | 16.8
Anorexia | 11.0 | 6.4
Dyspepsia | 6.7 | 4.5
Vomiting | 5.7 | 4.0
Endocrine System
Hot flushes | 66.5 | 59.4
Impotence | 11.0 | 12.9
Libido decreased | 11.0 | 4.5
Hemic and Lymphatic System
Anemia | 7.2 | 6.4
Metabolic and Nutritional System
Increased AST | 12.9 | 13.9
Peripheral edema | 12.4 | 17.3
Increased ALT | 9.1 | 8.9
Musculoskeletal System
Bone Pain | 6.2 | 5.0
Nervous System
Insomnia | 16.3 | 15.8
Dizziness | 10.0 | 11.4
Depression | 8.6 | 7.4
Hypesthesia | 5.3 | 2.0
Respiratory System
Dyspnea | 10.5 | 7.4
Upper respiratory infection | 8.1 | 10.9
Pneumonia | 5.3 | 3.5
Skin and Appendages
Sweating | 6.2 | 3.0
Body hair loss | 5.7 | 0.5
Dry skin | 5.3 | 2.5
Rash | 5.3 | 4.0
Special Senses
Impaired adaptation to dark | 56.9 | 5.4
Chromatopsia | 8.6 | 0.0
Impaired adaptation to light | 7.7 | 1.0
Abnormal vision | 6.2 | 4.5
Urogenital System
Testicular atrophy | 16.3 | 12.4
Gynecomastia | 10.5 | 11.9
Urinary tract infection | 8.6 | 21.3
Hematuria | 8.1 | 7.9
Urinary tract disorder | 7.2 | 10.4
Nocturia | 6.7 | 6.4

The overall incidence of adverse experiences is 99.5% (208/209) for the NILANDRON group and 98.5% (199/202) for the placebo group.

Some frequently occurring adverse experiences, for example hot flushes, impotence, and decreased libido, are known to be associated with low serum androgen levels and known to occur with medical or surgical castration alone. Notable was the higher incidence of visual disturbances (variously described as impaired adaptation to darkness, abnormal vision, and colored vision), which led to treatment discontinuation in 1% to 2% of patients.

Interstitial pneumonitis occurred in one (<1%) patient receiving NILANDRON in combination with surgical castration and in seven patients (3%) receiving NILANDRON in combination with leuprolide and one patient receiving placebo in combination with leuprolide. Overall, it has been reported in 2% of patients receiving NILANDRON. This included a report of interstitial pneumonitis in 8 of 47 patients (17%) in a small study performed in Japan.

In addition, the following adverse experiences were reported in 2 to 5% of patients treated with NILANDRON in combination with leuprolide or orchiectomy.

Body as a Whole: Malaise (2%).

Cardiovascular System: Angina (2%), heart failure (3%), syncope (2%).

Digestive System: Diarrhea (2%), gastrointestinal disorder (2%), gastrointestinal hemorrhage (2%), melena (2%).

Metabolic and Nutritional System: Alcohol intolerance (5%), edema (2%), weight loss (2%).

Musculoskeletal System: Arthritis (2%).

Nervous System: Dry mouth (2%), nervousness (2%), paresthesia (3%).

Respiratory System: Cough increased (2%), interstitial lung disease (2%), lung disorder (4%), rhinitis (2%).

Skin and Appendages: Pruritus (2%).

Special Senses: Cataract (2%), photophobia (2%).

Laboratory Values: Haptoglobin increased (2%), leukopenia (3%), alkaline phosphatase increased (3%), BUN increased (2%), creatinine increased (2%), hyperglycemia (4%).

To report SUSPECTED ADVERSE REACTIONS, contact Advanz Pharma (US) Corp. at 1-877-370-1142 or FDA at 1-800-FDA-1088 or www.fda.gov/medwatch.

OVERDOSAGE

One case of massive overdosage has been published. A 79-year-old man attempted suicide by ingesting 13 g of nilutamide (i.e., 43 times the maximum recommended dose). Despite immediate gastric lavage and oral administration of activated charcoal, plasma nilutamide levels peaked at 6 times the normal range 2 hours after ingestion. There were no clinical signs or symptoms or changes in parameters such as transaminases or chest X-ray. Maintenance treatment (150 mg/day) was resumed 30 days later.

In repeated-dose tolerance studies, doses of 600 mg/day and 900 mg/day were administered to 9 and 4 patients, respectively. The ingestion of these doses was associated with gastrointestinal disorders, including nausea and vomiting, malaise, headache, and dizziness. In addition, a transient elevation in hepatic enzyme levels was noted in one patient.

Since nilutamide is protein bound, dialysis may not be useful as treatment for overdose. As in the management of overdosage with any drug, it should be borne in mind that multiple agents may have been taken. If vomiting does not occur spontaneously, it should be induced if the patient is alert. General supportive care, including frequent monitoring of the vital signs and close observation of the patient, is indicated.

DOSAGE AND ADMINISTRATION

The recommended dosage is 300 mg once a day for 30 days, followed thereafter by 150 mg once a day. NILANDRON tablets can be taken with or without food.

HOW SUPPLIED

NILANDRON 150 mg tablets are supplied in boxes of 30 tablets. Each box contains 3 child-resistant, PVC, aluminum foil-backed blisters of 10 tablets (NDC 59212-111-14). Each white, biconvex, cylindrical (10 mm in diameter) tablet has a triangular logo on one side and an internal reference number (168D) on the other.

Store at 25°C (77°F); excursions permitted between 15-30°C (59-86°F) [see USP Controlled Room Temperature]. Protect from light. Keep out of reach of children.
Rev. 11/23
Manufactured for:
Advanz Pharma (US) Corp.
Bannockburn, IL 60015

NILANDRON® is a registered trademark of Mercury Pharma Group Limited. Distributed by Advanz Pharma (US) Corp. under license.

PRINCIPAL DISPLAY PANEL

NDC 59212-111-14

Nilandron® 150 mg
nilutamide
Tablets
150 mg

30 Tablets

ADVANZ PHARMA